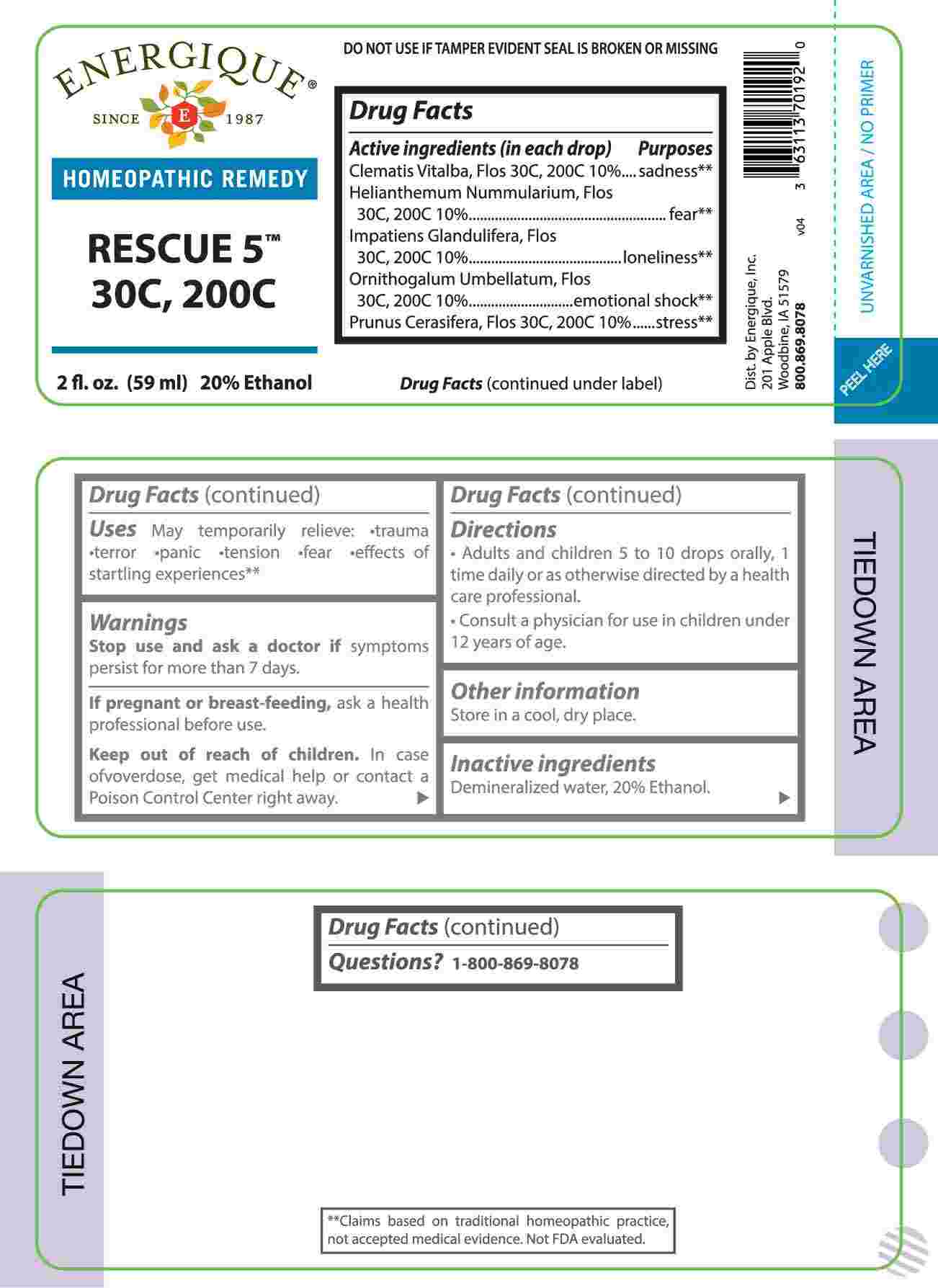 DRUG LABEL: Rescue 5
NDC: 44911-0238 | Form: LIQUID
Manufacturer: Energique, Inc.
Category: homeopathic | Type: HUMAN OTC DRUG LABEL
Date: 20241031

ACTIVE INGREDIENTS: CLEMATIS VITALBA FLOWER 30 [hp_C]/1 mL; HELIANTHEMUM NUMMULARIUM FLOWER 30 [hp_C]/1 mL; IMPATIENS GLANDULIFERA FLOWER 30 [hp_C]/1 mL; ORNITHOGALUM UMBELLATUM FLOWERING TOP 30 [hp_C]/1 mL; PRUNUS CERASIFERA FLOWER 30 [hp_C]/1 mL
INACTIVE INGREDIENTS: WATER; ALCOHOL

DRUG FACTS:

ACTIVE INGREDIENTS:

(in each drop) Clematis Vitalba, Flos 30C, 200C 10%, Helianthemum Nummularium, Flos 30C, 200C 10%, Impatiens Glandulifera, Flos 30C, 200C 10%, Ornithogalum Umbellatum, Flos 30C, 200C 10%, Prunus Cerasifera, Flos 30C, 200C 10%.

PURPOSE:

Clematis Vitalba, Flos – sadness,** Helianthemum Nummularium, Flos - fear,** Impatiens Glandulifera, Flos - loneliness,** Ornithogalum Umbellatum, Flos – emotional shock,** Prunus Cerasifera, Flos – stress**

**Claims based on traditional homeopathic practice, not accepted medical evidence. Not FDA evaluated.

USES:

May temporarily relieve: •trauma •terror •panic •tension •fear effects of startling experiences.**

**Claims based on traditional homeopathic practice, not accepted medical evidence. Not FDA evaluated.

WARNINGS:

Stop use and ask a doctor if symptoms persist for more than 7 days.

If pregnant or breast-feeding, ask a health professional before use.

Keep out of reach of children. In case of overdose, get medical help or contact a Poison Control Center right away.

DO NOT USE IF TAMPER EVIDENT SEAL IS BROKEN OR MISSING.

Store in a cool, dry place.

KEEP OUT OF REACH OF CHILDREN:

In case of overdose, get medical help or contact a Poison Control Center right away.

DIRECTIONS:

• Adults and children 5 to 10 drops orally, 1 time daily or as otherwise directed by a health care professional.

• Consult a physician for use in children under 12 years of age.

INACTIVE INGREDIENTS:

Demineralized water, 20% Ethanol.

QUESTIONS:

Dist. by Energique, Inc.

201 Apple Blvd

Woodbine, IA 51579

800-869-8078

PACKAGE LABEL DISPLAY:

ENERGIQUE

SINCE 1987

HOMEOPATHIC REMEDY

RESCUE 5

30C, 200C

2 fl. oz. (60 ml)